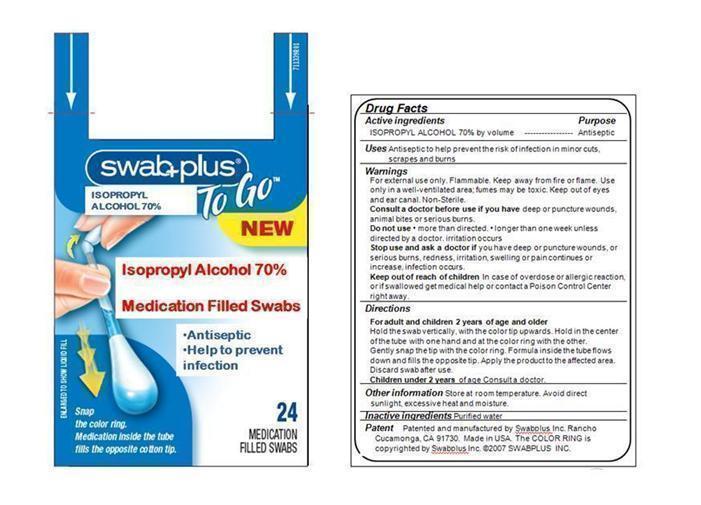 DRUG LABEL: Isopropyl Alcohol
NDC: 65734-101 | Form: SOLUTION
Manufacturer: Swabplus Inc.
Category: otc | Type: HUMAN OTC DRUG LABEL
Date: 20150227

ACTIVE INGREDIENTS: ISOPROPYL ALCOHOL 0.105 mL/0.15 mL
INACTIVE INGREDIENTS: Water

Isopropyl Alcohol 70% Filled Swab

Active ingredients

ISOPROPYL ALCOHOL 70%

Purpose

for Antiseptic

Uses

Uses First aid to help prevent infection, and temporarily relieve pain and itching associated with minor cuts, scrapes and burns.

Keep out of reach of children

If swallowed, get medical help or contact a Poison Control Center right away.

Directions

- Hold the swan vertically, with the color tip upwards. Hold in the center of the tube with one hand and at the color ring with the other.
- Gently snap the tip with the color ring. Formula inside the tube flows down and fills the opposite tip.
- Apply the product to the affected area.
- Discard swab after use.

Warnings

- For external use only. Keep out of eyes and ear canal. Non-Sterile. Discontinue use if irritation occurs.
- Do not use. longer than one week unless directed by a doctor.
- Stop use and ask a doctor if you have deep or puncture wounds, or serious burns, redness, irritation, swelling or pain continues or increase, infection occurs.

Administration

- For adult and children 2 and older:Clean affected area and apply 1 to 3 times daily. May be covered with a bandage.
- Children under 2 years of age: Do not use, consult a doctor.

Other information

Store at room temperature.Avoid direct sunlight, excessive heat and moistgure.

Inactive ingredients

Water

Patent

Patented and manufactured by Swabplus Inc. Rancho Cucamonga, CA 91730 Made in USA

The COLOR RING is copyrighted by Swabplus Inc. ©2007 SWABPLUS INC.

Package and Label

Image of Isopropyl Alcohol Label